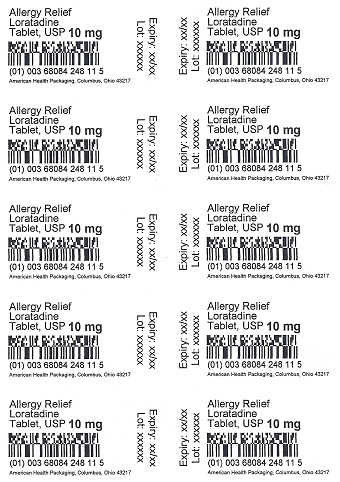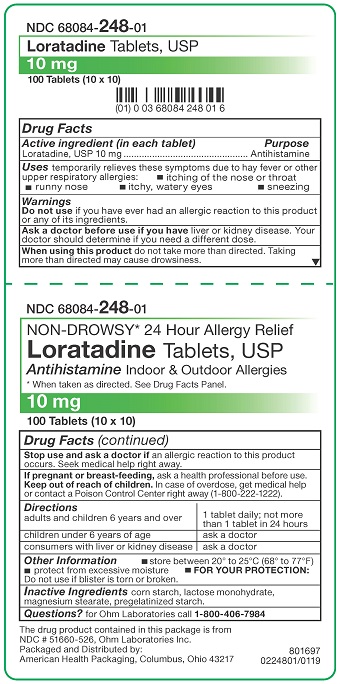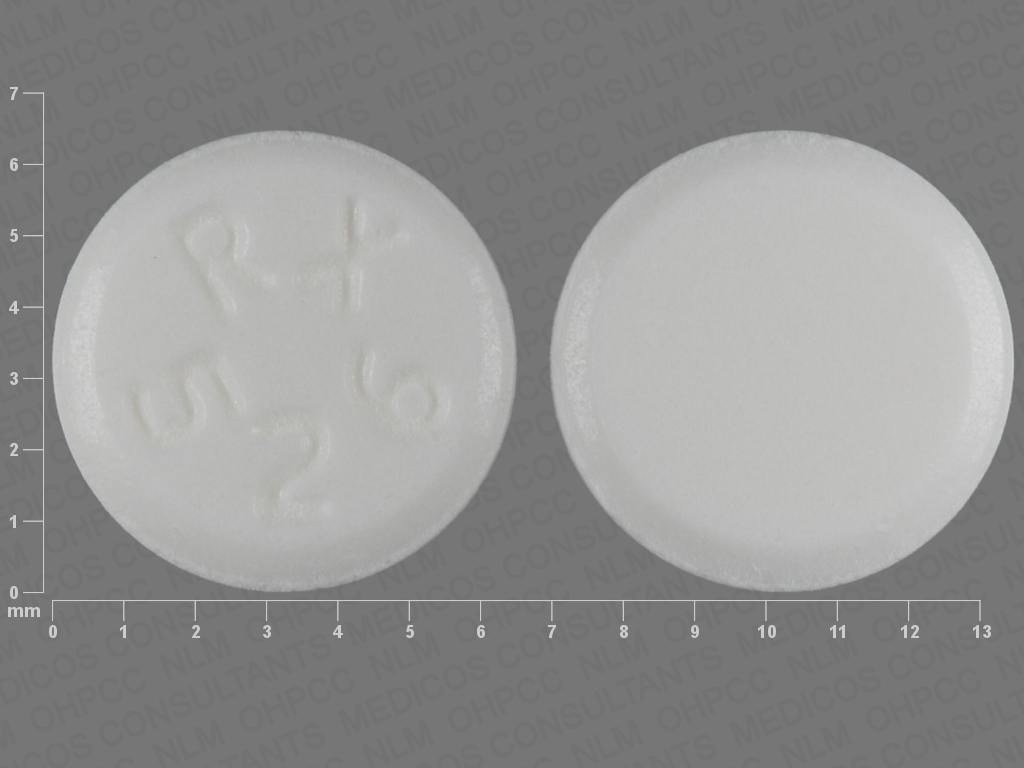 DRUG LABEL: Loratadine
NDC: 68084-248 | Form: TABLET
Manufacturer: American Health Packaging
Category: otc | Type: HUMAN OTC DRUG LABEL
Date: 20241121

ACTIVE INGREDIENTS: LORATADINE 10 mg/1 1
INACTIVE INGREDIENTS: STARCH, CORN; LACTOSE MONOHYDRATE; MAGNESIUM STEARATE

Loratadine Tablets, USP Antihistamine
Drug Facts

Active ingredient (in each tablet)

Loratadine USP, 10 mg

Purpose

Antihistamine

Uses

temporarily relieves these symptoms due to hay fever or other upper respiratory allergies:

- itching of the nose or throat
- runny nose
- itchy, watery eyes
- sneezing

Warnings

Do not use

if you have ever had an allergic reaction to this product or any of its ingredients.

Ask a doctor before use if you have

liver or kidney disease. Your doctor should determine if you need a different dose.

When using this product

do not take more than directed. Taking more than directed may cause drowsiness.

Stop use and ask a doctor if

an allergic reaction to this product occurs. Seek medical help right away.

If pregnant or breast-feeding,

ask a health professional before use.

Keep out of reach of children.

In case of overdose, get medical help or contact a Poison Control Center right away (1-800-222-1222).

Directions

adults and children 6 years and over | 1 tablet daily; not more than 1 tablet in 24 hours
children under 6 years of age | ask a doctor
consumers with liver or kidney disease | ask a doctor

Other Information

- store between 20° to 25°C (68° to 77°F)
- protect from excessive moisture
- FOR YOUR PROTECTION: Do not use if blister is torn or broken.

Inactive Ingredients

Corn starch, lactose monohydrate, magnesium stearate, pregelatinized starch

Questions?

for Ohm Laboratories call 1-800-406-7984

The drug product contained in this package is from NDC # 51660-526, Ohm Laboratories Inc.

Packaged and Distributed by:
American Health Packaging, Columbus, Ohio 43217

Principal Display Panel – Carton – 10 mg

NDC 68084- 248-01

NON-DROWSY* 24 Hour Allergy Relief
Loratadine Tablets, USP

Antihistamine Indoor & Outdoor Allergies

10 mg

100 Tablets (10 x 10)

* When taken as directed. See Drug Facts Panel.

The drug product contained in this package is from
NDC # 51660-526, Ohm Laboratories Inc.

Packaged and Distributed by:
American Health Packaging, Columbus, Ohio 43217

801697
0224801/0119

Principal Display Panel – Blister – 10 mg

Allergy Relief
Loratadine
Tablet, USP 10 mg